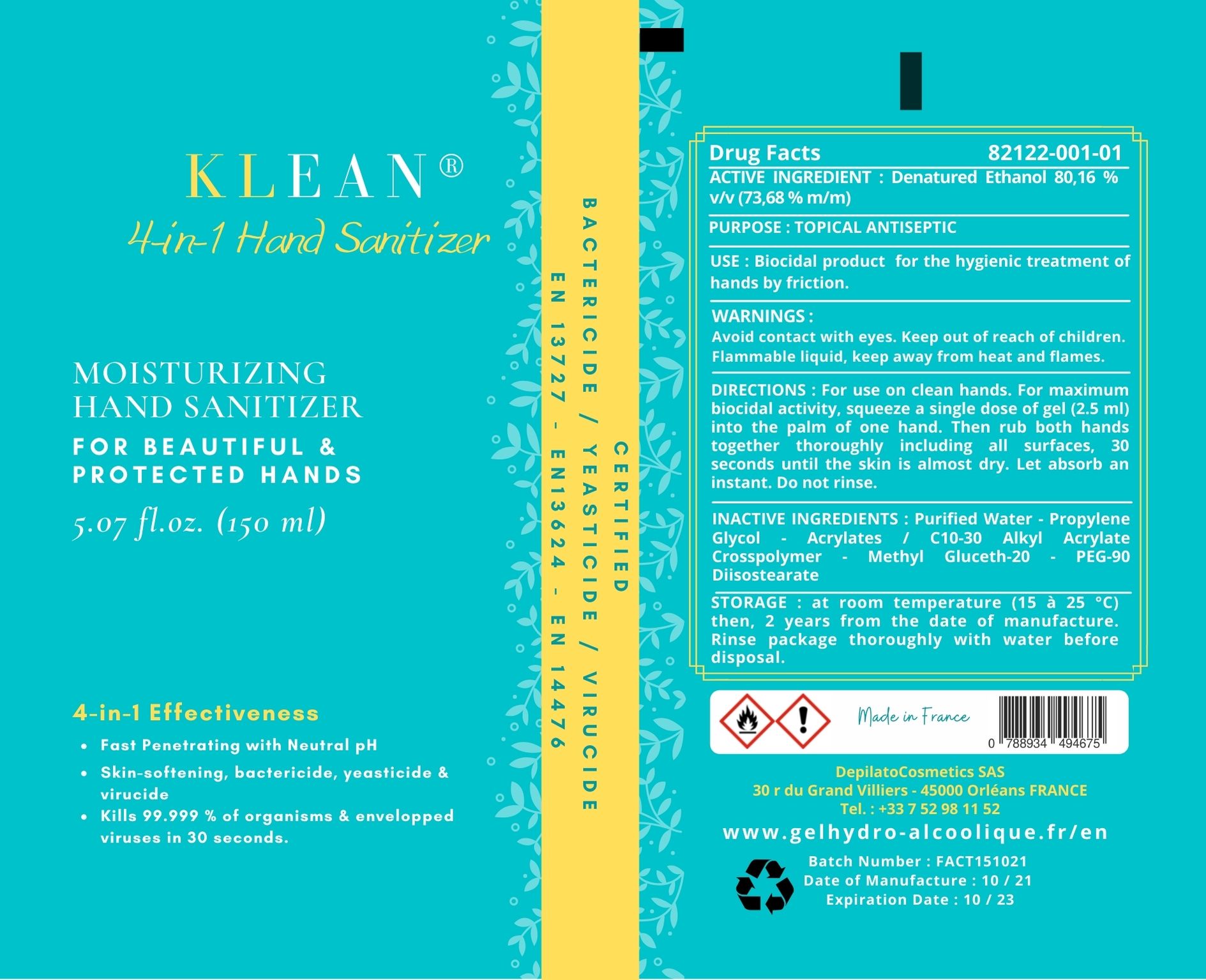 DRUG LABEL: KLEAN 4-IN-1 Hand Sanitizer
NDC: 82122-001 | Form: GEL
Manufacturer: DepilatoCosmetics SAS
Category: otc | Type: HUMAN OTC DRUG LABEL
Date: 20210829

ACTIVE INGREDIENTS: ALCOHOL 73.68 g/100 g
INACTIVE INGREDIENTS: PROPYLENE GLYCOL 0.8 g/100 g; CARBOMER INTERPOLYMER TYPE A (55000 CPS) 0.35 g/100 g; WATER 24.68 g/100 g; METHYL GLUCETH-20 0.13 g/100 g; PEG-90 DIISOSTEARATE 0.25 g/100 g; AMINOMETHYLPROPANOL 0.11 g/100 g

Purpose :

Antiseptic

Active Ingredient :

Alcohol 80.00 % v/v.

Use :

Hand Sanitizer for the hygenic treatment of hands by friction. For use when soap and water are not available.

Warnings :

Avoid contact with eyes. For external use only. Flammable. Keep away from heat or flame

Keep out of reach of children. If swallowed, get medical help or contact a Poison Control Center right away.

Directions

For use on clean hands. For maximum biocidal activity, pump a single dose of gel (2. 5 ml) into the palm of one hand. Then rub both hands together thoroughly including all surfaces, 30 seconds until the skin is almost dry. Let absorb an instant. Do not rinse.

Storage :

at room temperature (15 à 25 °C) 2 years from the date of manufacture. Rinse package thoroughly with water before disposal.

Inactive ingredients :

Purified Water - Propylene Glycol - Acrylates / C10-30 Alkyl Acrylate Crosspolymer - Methyl Gluceth-20 - PEG-90 Diisostearate

Package Label - Principal Display Panel

0.175 L (175 mL) NDC: 82122-001-01